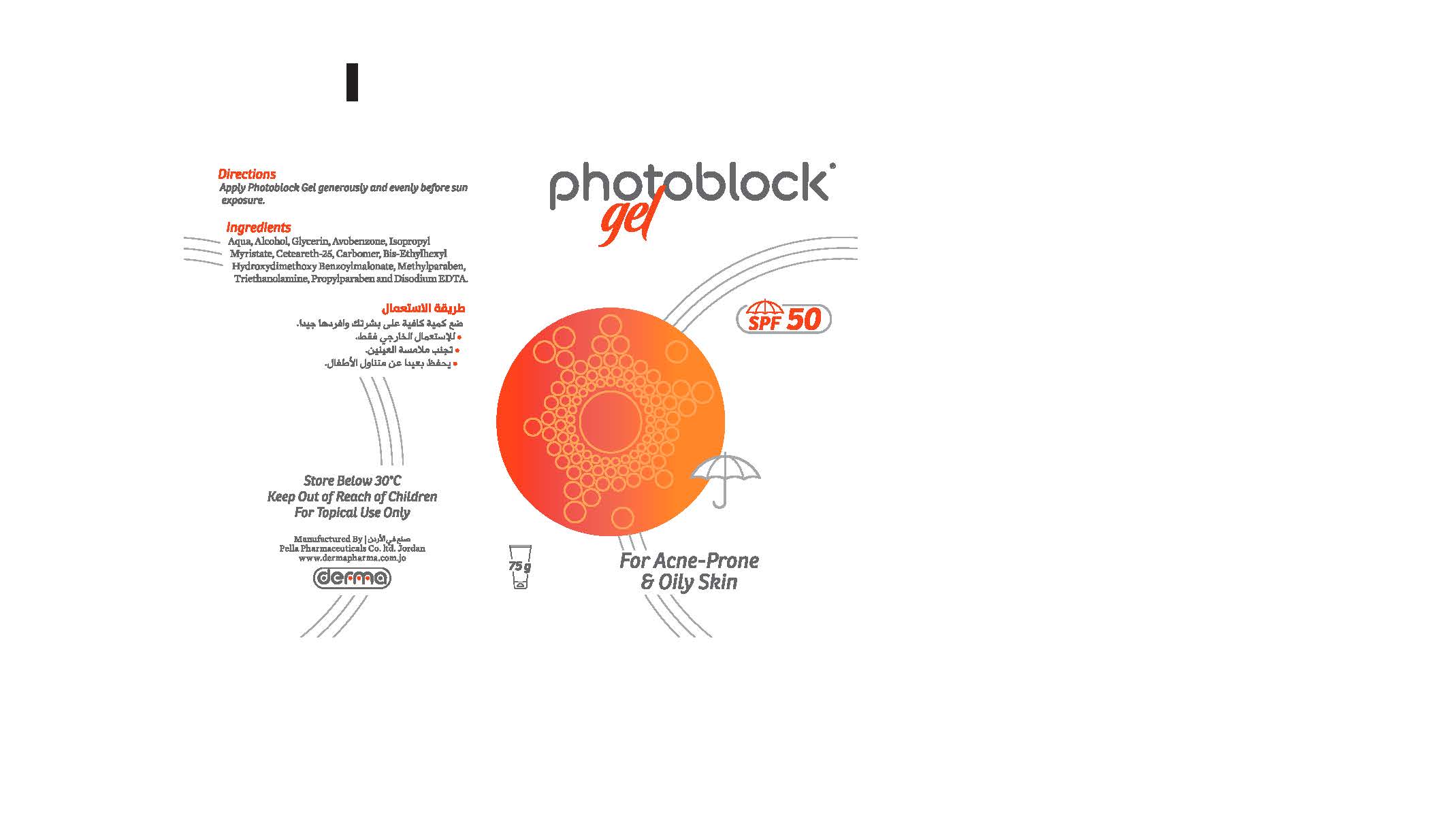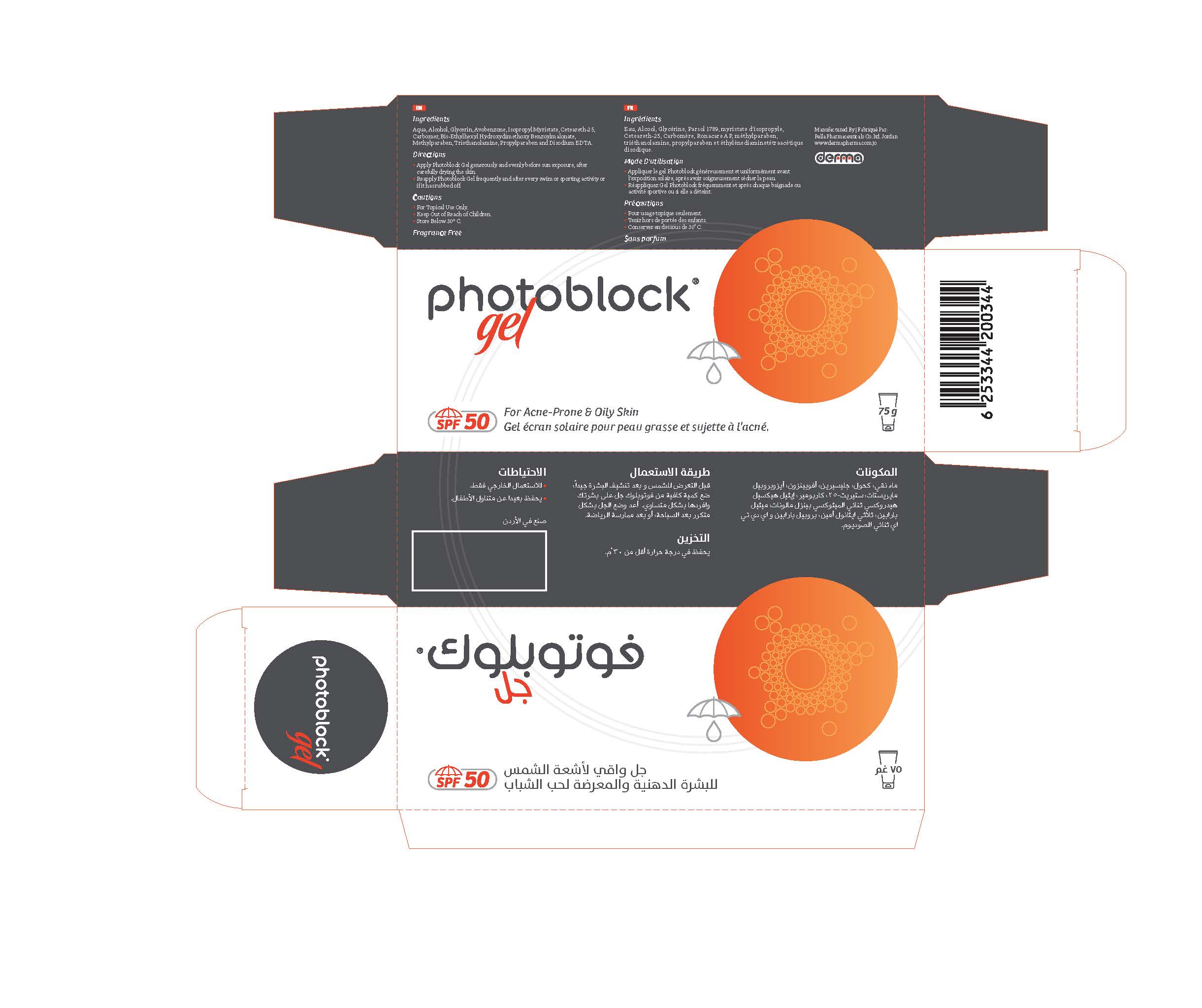 DRUG LABEL: Photoblock
NDC: 82160-344 | Form: GEL
Manufacturer: Pella Pharmaceuticals Co. Ltd
Category: otc | Type: HUMAN OTC DRUG LABEL
Date: 20211124

ACTIVE INGREDIENTS: BIS-ETHYLHEXYL HYDROXYDIMETHOXY BENZYLMALONATE 3.75 mg/75 g; AVOBENZONE 30 mg/75 g
INACTIVE INGREDIENTS: EDETATE DISODIUM ANHYDROUS; ALCOHOL; METHYLPARABEN; TROLAMINE; PROPYLPARABEN; GLYCERIN; ISOPROPYL MYRISTATE; CETEARETH-25; WATER; CARBOMER 940

Photo Gel

Forms and Presentation

Gel: Tube of 75 g.

Active ingredients

Avobenzone

Bis-Ethylhexyl Hydroxydimethoxy Benzylmalonate

Inactive Ingredients

Aqua, Alcohol, Glycerin, Isopropyl Myristate, Ceteareth-25, Carbomer, Methylparaben, Triethanolamine, Propylparaben and Disodium EDT A.

Purpose

Sunscreen

Properties

Photoblock ® Gel is a gel sunscreen with a protection factor SPF 50. The Photoblock® Gel sunscreen is distinguished by its special formula; it is suitable for oily and acne-prone skin, Photoblock® Gel provides long-term protection during times of peak temperatures during the day.

Indications

Photoblock® Gel with its protection SPF 50 is recommended for oily and acne-prone skin.

Precautions

Keep out of reach of children

Warnings

- For external use only
- Avoid contact with eyes

Contraindications

Hypersensitivity to any of the components.

Side effects

Photoblock® Gel has no known side effects, its use is harmless.

Dosage and administration

Apply Photoblock® Gel before sun exposure and on dry skin, apply a sufficient amount of Photoblock® Gel and spread it well on the whole area.
Reapply every 2 hours or after swimming or sports.

Storage conditions

Store at a temperature below 30 ° C.